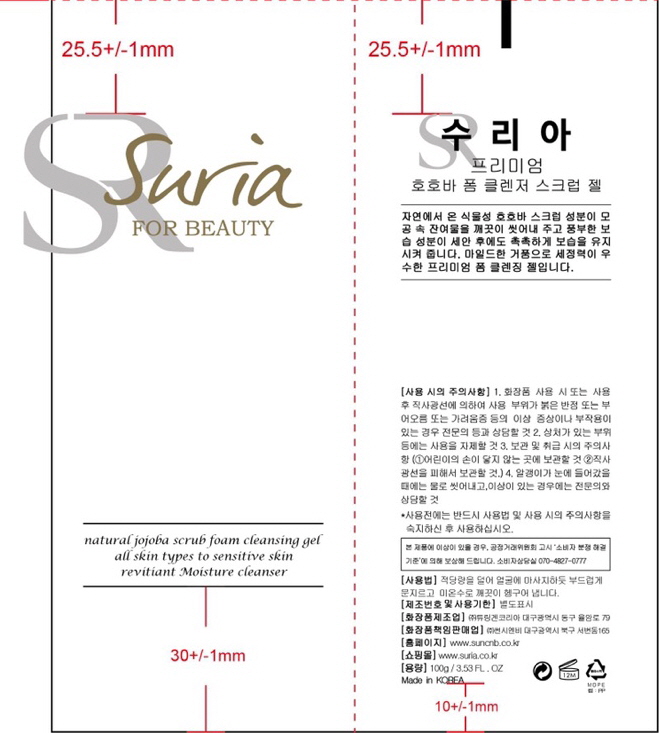 DRUG LABEL: SURIA PREMIUM JOJOBA FOAM CLEANSER
NDC: 81479-002 | Form: LIQUID
Manufacturer: SUN C&B
Category: otc | Type: HUMAN OTC DRUG LABEL
Date: 20210203

ACTIVE INGREDIENTS: GLYCERIN 4 g/100 mL
INACTIVE INGREDIENTS: WATER 96 g/100 mL

ACTIVE INGREDIENT

GLYCERIN

INACTIVE INGREDIENT

Water,ETC

Keep out of reach of children. If swallowed, get medical help or contact a Poison Control Center.

Do not use if you are allergic to any ingredients.

WARNINGS

For External Use Only. Do not ingest

PURPOSE

Cleansing

Dosage and administration:Take appropriate amount according to your skin condition and apply every morning and night.

INDICATIONS AND USAGE

Indication and usage:Following emulsion, pour some on the palm of your hand and apply to skin gently. Press down lightly until absorbed.